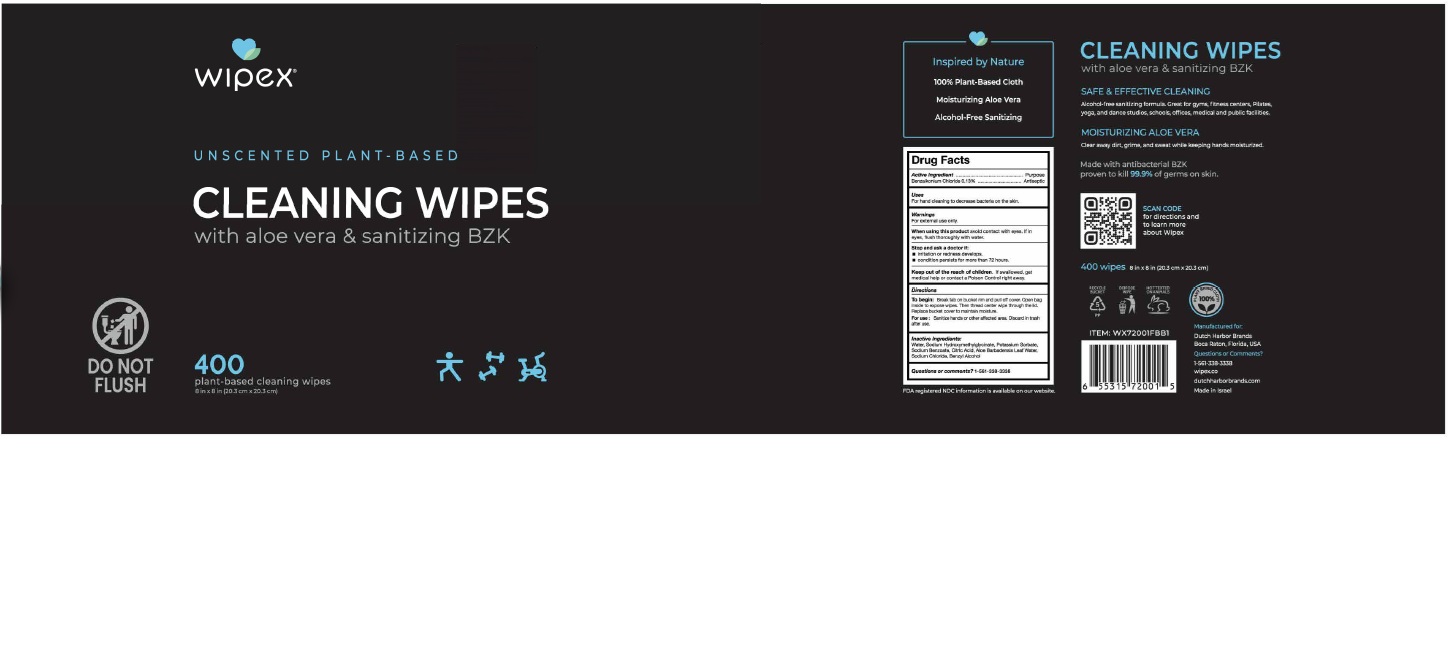 DRUG LABEL: Wipex
NDC: 74680-201 | Form: CLOTH
Manufacturer: Unico International Trading Corporation
Category: otc | Type: HUMAN OTC DRUG LABEL
Date: 20260108

ACTIVE INGREDIENTS: BENZALKONIUM CHLORIDE 1.3 mg/1 mL
INACTIVE INGREDIENTS: SODIUM BENZOATE; SODIUM CHLORIDE; CITRIC ACID MONOHYDRATE; POTASSIUM SORBATE; SODIUM HYDROXYMETHYLGLYCINATE; ALOE VERA LEAF; WATER

Wipex

Active Ingredient

Benzalkonium chloride 0.13%

Keeo Out of the Reach of Children

Keep out of the reach of children. If swallowed, get medical help or contact a Poison Contrl right away.

Warning

For external use only. Avoid cntact with the eyes. If in eyes, flush thoroughly with water.

Inactive Ingredients

Sodium benzoate, sodium chloride, citric acid, potassium sorbate, sodium hydroxymethylglycinate, aloe vera, water

Purpose

Antiseptic

To disperse

To begin: Break tab on bucket rim and pull off cover. Open bag inside to expose wipes, then thread center wipe through the lid. Replace bucket cover to maintain moisture.

Stop Use

Stop and ask a doctor if:

Irritation or redness developes.

Conditions persists for more than 72 hours.

To Use

Sanitize hands or other affected area. Discard in trash after use.